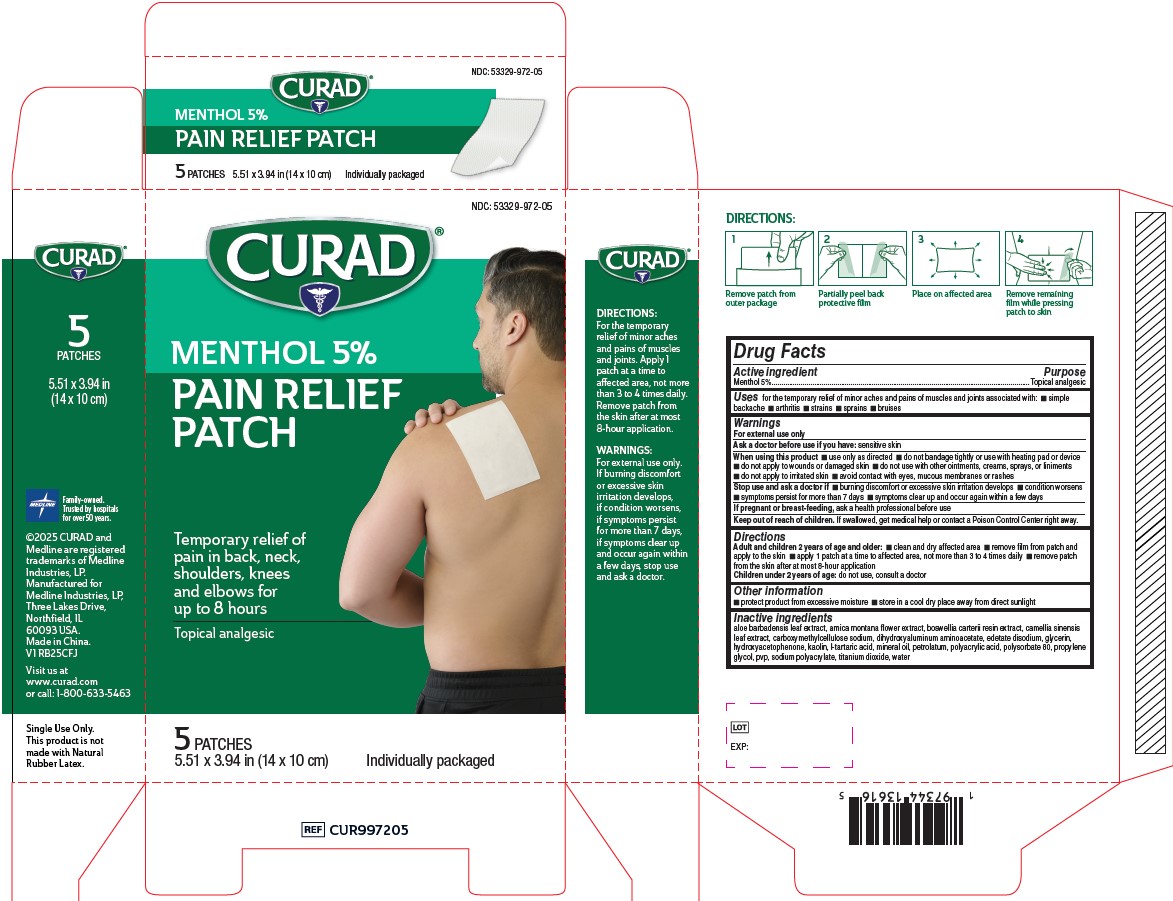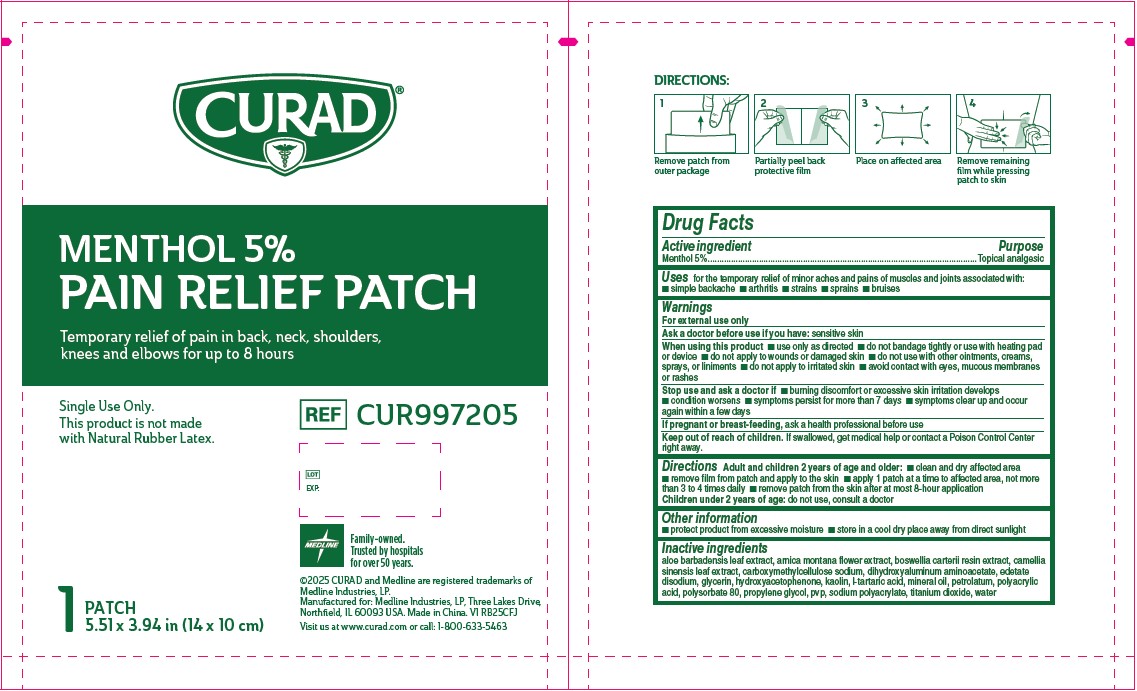 DRUG LABEL: Medline
NDC: 53329-972 | Form: PATCH
Manufacturer: Medline Industries, LP
Category: otc | Type: HUMAN OTC DRUG LABEL
Date: 20250626

ACTIVE INGREDIENTS: MENTHOL 5 mg/100 mg
INACTIVE INGREDIENTS: ARNICA MONTANA FLOWER; EDETATE DISODIUM; POLYACRYLIC ACID (250000 MW); TITANIUM DIOXIDE; PROPYLENE GLYCOL; HYDROXYACETOPHENONE; POLYSORBATE 80; PETROLATUM; PVP; WATER; MINERAL OIL; CAMELLIA SINENSIS LEAF; SODIUM POLYACRYLATE (8000 MW); DIHYDROXYALUMINUM AMINOACETATE; CARBOXYMETHYLCELLULOSE SODIUM; FRANKINCENSE; KAOLIN; TARTARIC ACID, MESO-; ALOE BARBADENSIS LEAF; GLYCERIN

972 Medline 5% Menthol Pain Relief Patch

Active ingredient

Menthol 5%

Purpose

Topical analgesic

Uses

for the temporary relief of minor aches and pains of muscles and joints associated with:

- simple backache
- arthritis
- strains
- sprains
- bruises

Warnings

For external use only

Ask doctor before use if you have:

sensitive skin

When using this product

- use only as directed
- do not bandage tightly or use with heating pad or device
- do not apply to wounds or damaged skin
- do not use with other ointments, creams, sprays, or liniments
- do not apply to irritated skin
- avoid contact with eyes, mucous membranes or rashes

Stop use and ask a doctor if

- burning discomfort or excessive skin irritation develops
- condition worsens
- symptoms persist for more than 7 days
- symptoms clear up and occur again within a few days

If pregnant or breast-feeding,

ask a health professional before use

Keep out of reach of children.

If swallowed, get medical help or contact a Poison Control Center right away.

Directions

Adult and children 2 years of age and older:

- clean and dry affected area
- remove film from patch and apply to the skin
- apply 1 patch at a time to affected area, not more than 3 to 4 times daily
- remove patch from the skin after at most 8-hour application

Children under 2 years of age: do not use, consult a doctor

Other information

- protect product from excessive moisture
- store in a cool dry place away from direct sunlight

Inactive ingredients

aloe barbadensis leaf extract, arnica montana flower extract, boswellia carterii resin extract, camellia sinensis leaf extract, carboxymethylcellulose sodium, dihydroxyaluminum aminoacetate, edetate disodium, glycerin, hydroxyacetophenone, kaolin, l-tartaric acid, mineral oil, petrolatum, polyacrylic acid, polysorbate 80, propylene glycol, pvp, sodium polyacrylate, titanium dioxide, water

Manufacturer information

©2025 CURAD and Medline are registered trademarks of Medline Industries, LP.
Manufactured for Medline Industries, LP,
Three Lakes Drive, Northfield, IL 60093 USA.
Made in China.
Ref. CUR997205 V1 RB25CFJ